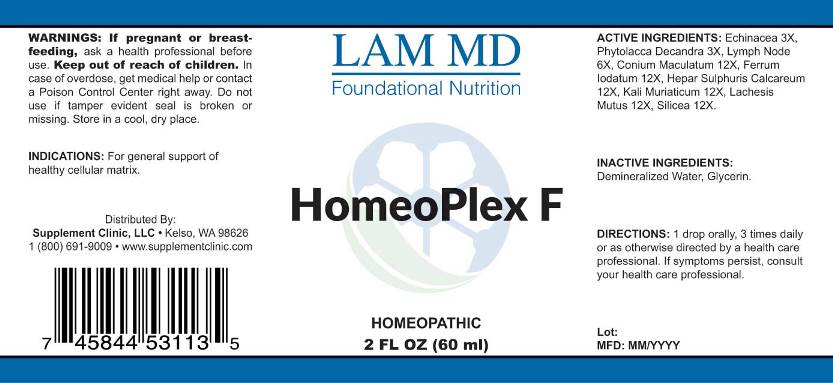 DRUG LABEL: Homeoplex F
NDC: 71781-0004 | Form: LIQUID
Manufacturer: Supplement Clinic, LLC.
Category: homeopathic | Type: HUMAN OTC DRUG LABEL
Date: 20171101

ACTIVE INGREDIENTS: ECHINACEA ANGUSTIFOLIA 3 [hp_X]/1 mL; PHYTOLACCA AMERICANA ROOT 3 [hp_X]/1 mL; SUS SCROFA LYMPH 6 [hp_X]/1 mL; CONIUM MACULATUM FLOWERING TOP 12 [hp_X]/1 mL; FERROUS IODIDE 12 [hp_X]/1 mL; CALCIUM SULFIDE 12 [hp_X]/1 mL; POTASSIUM CHLORIDE 12 [hp_X]/1 mL; LACHESIS MUTA VENOM 12 [hp_X]/1 mL; SILICON DIOXIDE 12 [hp_X]/1 mL
INACTIVE INGREDIENTS: WATER; GLYCERIN

Drug Facts:

ACTIVE INGREDIENTS:

Echinacea (Angustifolia) 3X, Phytolacca Decandra 3X, Lymph Node (Suis) 6X, Conium Maculatum 12X, Ferrum Iodatum 12X, Hepar Sulphuris Calcareum 12X, Kali Muriaticum 12X, Lachesis Mutus 12X, Silicea 12X.

INDICATIONS:

For general support of healthy cellular matrix.

WARNINGS:

If pregnant or breast-feeding, ask a health professional before use.
Keep out of reach of children. In case of overdose, get medical help or contact a Poison Control Center right away.
Do not use if tamper evident seal is broken or missing.
Store in cool, dry place.

Keep out of reach of children. In case of overdose, get medical help or contact a Poison Control Center right away.

DIRECTIONS:

1 drop orally, 3 times daily or as otherwise directed by a health care professional. If symptoms persist, consult your health care professional.

INDICATIONS:

For general support of healthy cellular matrix.

INACTIVE INGREDIENTS:

Demineralized Water, Glycerin

QUESTIONS:

Distributed By:
Supplement Clinic, LLC. • Kelso, WA 98626
1(800)691-9009 • www.supplementclinic.com

PACKAGE LABEL DISPLAY:

LAM MD
Foundational Nutrition

HomeoPlex F

HOMEOPATHIC
2 FL OZ (60 ml)